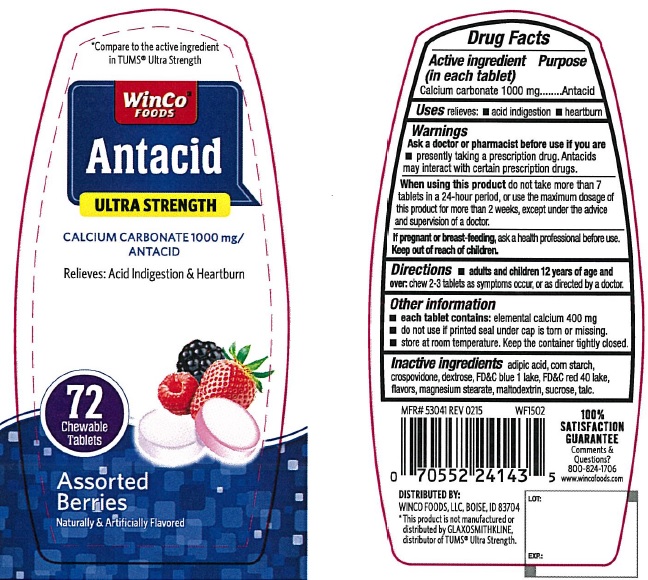 DRUG LABEL: Antacid Ultra Strength Assorted Berries
NDC: 67091-226 | Form: TABLET, CHEWABLE
Manufacturer: WinCo Foods, LLC
Category: otc | Type: HUMAN OTC DRUG LABEL
Date: 20220114

ACTIVE INGREDIENTS: CALCIUM CARBONATE 1000 mg/1 1
INACTIVE INGREDIENTS: ADIPIC ACID; STARCH, CORN; CROSPOVIDONE; DEXTROSE, UNSPECIFIED FORM; FD&C BLUE NO. 1; FD&C RED NO. 40; MAGNESIUM STEARATE; MALTODEXTRIN; SUCROSE; TALC

Antacid Ultra Strength Assorted Berries

Active ingredient (in each tablet)

Calcium carbonate 1000 mg

Purpose

Antacid

Uses

relieves

- acid indigestion
- heartburn

Warnings

Ask a doctor or pharmacist before use if you are

- presently taking a prescription drug. Antacids may interact with certain prescription drugs.

When using this product

do not take more than 7 tablets in a 24-hour period, or use the maximum dosage of this product for more than 2 weeks, except under the advice and supervision of the a doctor.

Keep out of reach of children

Directions

- chew 2-3 tablets as symptoms occur, or as directed by a doctor.

Other information

- each tablet contains: calcium 400 mg
- do not use if printed seal under cap is torn or missing
- store at room temperature. keep the container tightly closed.

Inactive ingredients

adipic acid, corn starch, crospovidone, dextrose, FD&C Blue 1 lake, FD&C Red 40 lake, flavors, magnesium stearate, maltodextrin, sucrose, talc

Principal Display Panel

*Compare to the Active ingredient in TUMS® Ultra strength

WinCo Foods

Antacid Ultra Strength

CALCIUM CARBONATE 1000 mg/ANTACID

Relieves: Acid Indigestion & Heartburn

Assorted Berries

Naturally and Artificially Flavored

72 CHEWABLE TABLETS